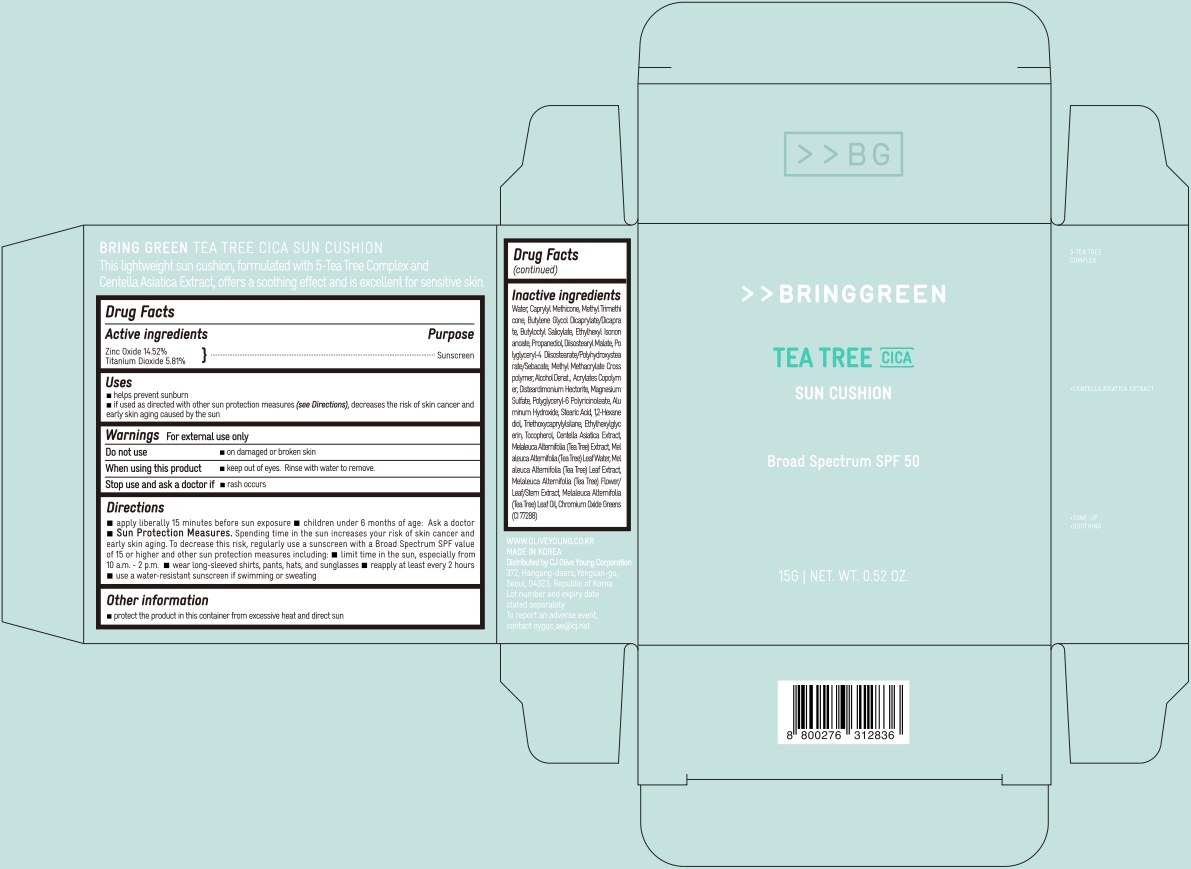 DRUG LABEL: BRING GREEN TEA TREE CICA SUN CUSHION
NDC: 81540-101 | Form: CREAM
Manufacturer: CJ Olive Young Corporation
Category: otc | Type: HUMAN OTC DRUG LABEL
Date: 20251117

ACTIVE INGREDIENTS: TITANIUM DIOXIDE 0.8715 g/15 g; ZINC OXIDE 2.178 g/15 g
INACTIVE INGREDIENTS: MELALEUCA ALTERNIFOLIA FLOWERING TOP; 1,2-HEXANEDIOL; MELALEUCA ALTERNIFOLIA (TEA TREE) LEAF OIL; METHYL METHACRYLATE/GLYCOL DIMETHACRYLATE CROSSPOLYMER; POLYGLYCERYL-4 DIISOSTEARATE/POLYHYDROXYSTEARATE/SEBACATE; CENTELLA ASIATICA TRITERPENOIDS; CAPRYLYL METHICONE; BUTYLENE GLYCOL DICAPRYLATE/DICAPRATE; DISTEARDIMONIUM HECTORITE; ALUMINUM HYDROXIDE; MAGNESIUM SULFATE; ALCOHOL; POLYGLYCERYL-6 POLYRICINOLEATE; ETHYLHEXYLGLYCERIN; ETHYLHEXYL ISONONANOATE; PROPANEDIOL; BUTYL ACRYLATE/METHYL METHACRYLATE/METHACRYLIC ACID COPOLYMER (18000 MW); STEARIC ACID; BUTYLOCTYL SALICYLATE; DIISOSTEARYL MALATE; MELALEUCA ALTERNIFOLIA (TEA TREE) LEAF; CHROMIUM OXIDE GREENS; WATER; METHYL TRIMETHICONE; TRIETHOXYCAPRYLYLSILANE; TOCOPHEROL

81540-101 BRING GREEN TEA TREE CICA SUN CUSHION

ACTIVE INGREDIENT

Zinc Oxide 14.52%

Titanium Dioxide 5.81%

PURPOSE

Sunscreen

Uses

■ helps prevent sunburn

■ If used as directed with other sun protection measures (see Directions), decreases the risk of skin cancer and early skin aging caused by the skin

Warnings

For external use only

Do not use ■ on damaged or broken skin

When using this product ■ keep out of eyes. Rinse with water to remove

Stop use and ask a doctor if ■ rash occurs

Directions

■ apply liberally 15 minutes before sun exposure ■ children under 6 months of age: Ask a doctor ■ Sun Protection Measures. Spending time in the sun increases your risk of skin cancer and early skin aging. To decrease this risk, regularly use a sunscreen with a Broad Spectrum SPF value of 15 or higher and other sun protection measures including: ■ limit time in the sun, especially from 10 a.m. - 2 p.m. ■ wear long-sleeved shirts, pants, hats, and sunglasses reapply at least every 2 hours ■ use a water-resistant sunscreen if swimming or sweating

OTHER SAFETY INFORMATION

■ protect the product in this container from excessive heat and direct sun

■ keep out of reach of children

INACTIVE INGREDIENT

Water, Caprylyl Methicone, Methyl Trimethi cone, Butylene Glycol Dicaprylate/Dicaprate, Butyloctyl Salicylate, Ethylhexyl Isononanoate, Propanediol, Diisostearyl Malate, Polyglyceryl-4 Diisostearate/Polyhydroxystearate/Sebacate, Methyl Methacrylate Cross polymer, Alcohol Denat., Acrylates Copolymer, Disteardimonium Hectorite, Magnesium Sulfate, Polyglyceryl-6 Polyricinoleate, Aluminum Hydroxide, Stearic Acid, 1,2-Hexanediol, Triethoxycaprylylsilane, Ethylhexylglycerin, Tocopherol, Centella Asiatica Extract, Melaleuca Alternifolia (Tea Tree) Extract, Melaleuca Alternifolia (Tea Tree) Leaf Water, Melaleuca Alternifolia (Tea Tree) Leaf Extract, Melaleuca Alternifolia (Tea Tree) Flower/ Leaf/Stem Extract, Melaleuca Alternifolia (Tea Tree) Leaf Oil, Chromium Oxide Greens (CI 77288)